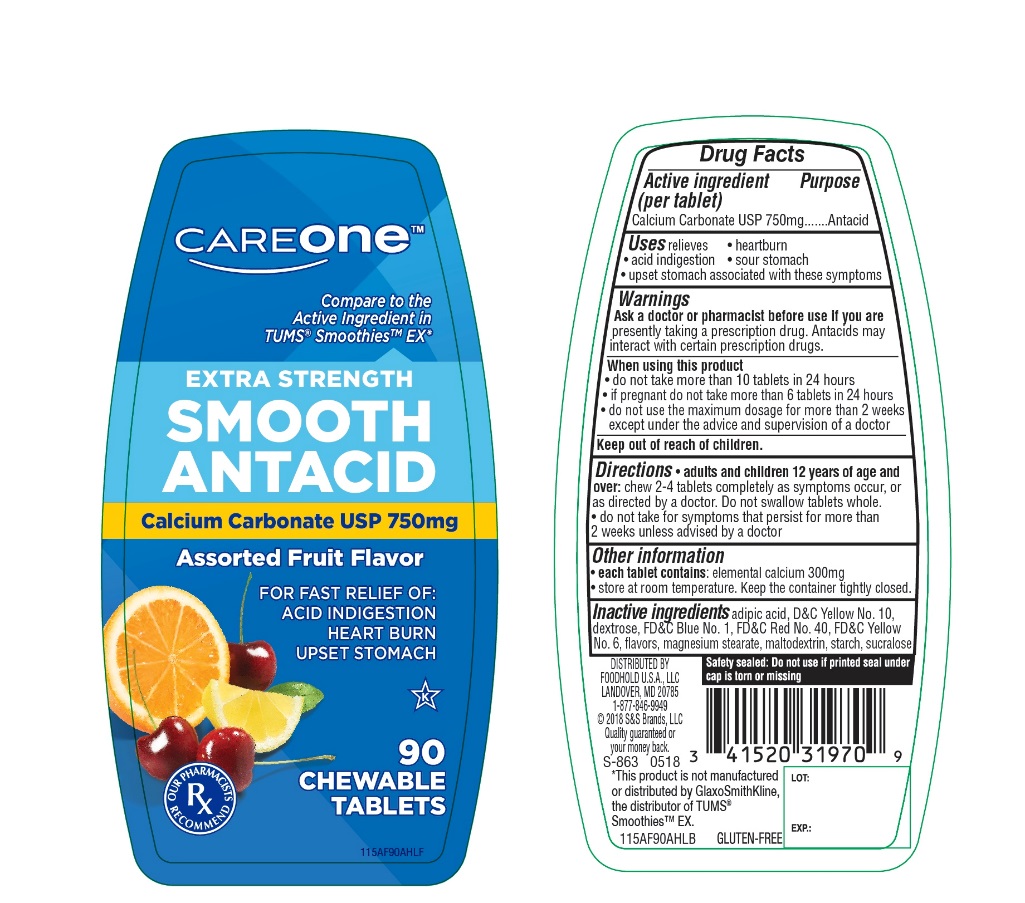 DRUG LABEL: CAREONE Extra Strength

NDC: 41520-905 | Form: TABLET, CHEWABLE
Manufacturer: FOODHOLD USA
Category: otc | Type: HUMAN OTC DRUG LABEL
Date: 20250718

ACTIVE INGREDIENTS: CALCIUM CARBONATE 750 mg/1 1
INACTIVE INGREDIENTS: ADIPIC ACID; D&C YELLOW NO. 10; DEXTROSE, UNSPECIFIED FORM; FD&C BLUE NO. 1; FD&C RED NO. 40; FD&C YELLOW NO. 6; MAGNESIUM STEARATE; MALTODEXTRIN; STARCH, CORN; SUCRALOSE

Extra Strength Smooth Antacid Assorted Fruit 90 Chewable Tablets

Active ingredient (per tablet)

Calcium Carbonate 750 mg

Purpose

Antacid

Uses

relieves:

- heartburn
- acid indigestion
- sour stomach
- upset stomach associated with these symptoms

Ask a doctor or pharmacist before use if you are

- presently taking a prescription drug. Antacids may interact with certain prescription drugs.

When using this product

- do not take more than 10 tablets in a 24-hours
- if pregnant do not take more than 6 tablets in 24 hours
- do not use the maximum dosage for more than 2 weeks except under the advice and supervision of a doctor.

Directions

- adults and children 12 years of age and over:chew 2-4 tablets as symptoms occur, or as directed by a doctor. Do not swallow tablets whole
- do not take for symptoms that persists for more than 2 weeks unless advised by a doctor

Other information

- each tablet contains : elemental calcium 300 mg
- store at room temperature. Keep the container tightly closed.

SAFETY SEALED: DO NOT USE IF PRINTED SEAL UNDER CAP IS TORN OR MISSING

Inactive ingredients

adipic acid, D&C Yellow No. 10, dextrose, FD&C Blue No. 1, FD&C Red No. 40, FD&C Yellow No. 6 flavors, magnesium stearate, maltodextrin, starch, sucralose

PRINCIPAL DISPLAY PANEL

CAREONE™

NDC 41520-905-90

Compare to the Active Ingredient in TUMS®Smoothies™ EX*

EXTRA STRENGTH

SMOOTH ANTACID

Calcium Carbonate USP 750 mg

Assorted Fruit Flavors

FOR FAST RELIEF OF:

- ACID INDIGESTION
- HEARTBURN
- UPSET STOMACH

90 CHEWABLE TABLETS

GLUTEN-FREE

DISTRIBUTED. BY:

FOODHOLD U.S.A., LLC

LANDOVER, MD 20785

1-877-846-9949

© 2018 S&S Brands, LLC, Quality guaranteed or your money back.

*This product is not manufactured or distributed by GlaxoSmithKline, the distributor of TUMS® Smoothies™EX..